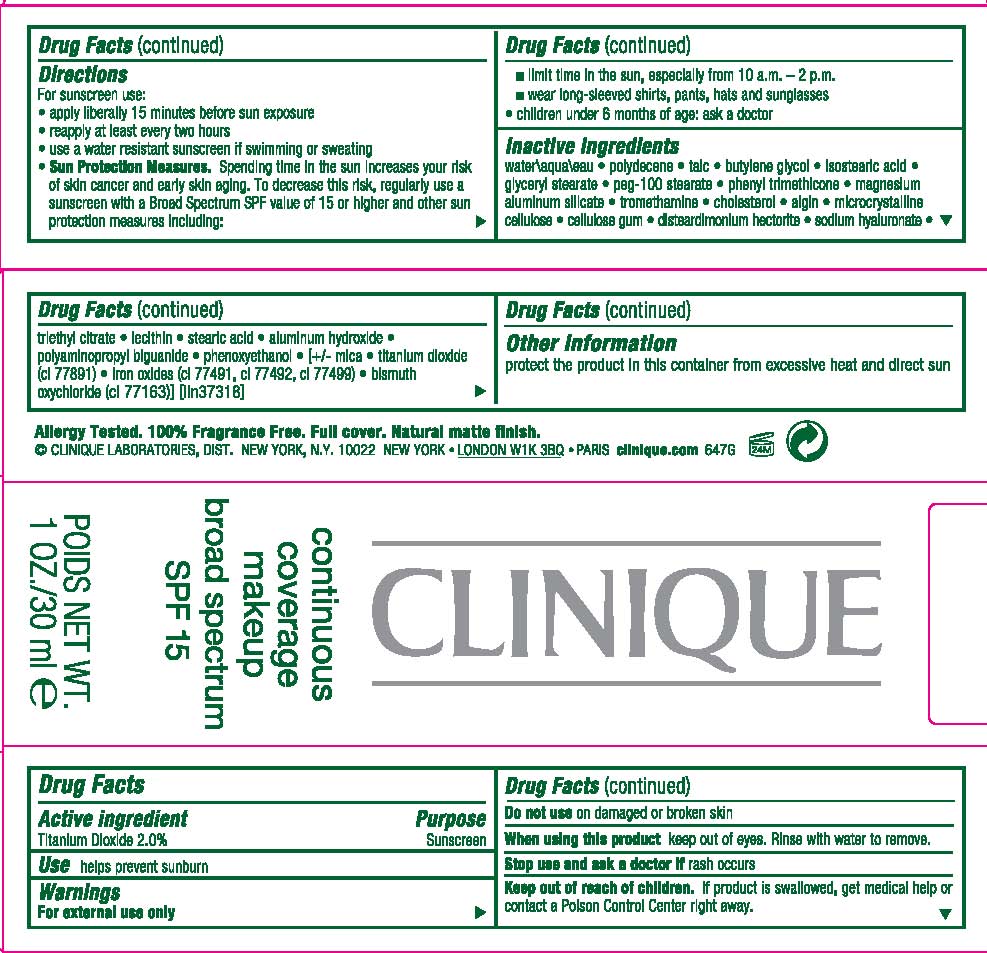 DRUG LABEL: CONTINUOUS COVERAGE MAKEUP
NDC: 49527-010 | Form: CREAM
Manufacturer: CLINIQUE LABORATORIES INC
Category: otc | Type: HUMAN OTC DRUG LABEL
Date: 20111219

ACTIVE INGREDIENTS: TITANIUM DIOXIDE 2.0 mL/100 mL
INACTIVE INGREDIENTS: WATER; TALC; BUTYLENE GLYCOL; ISOSTEARIC ACID; GLYCERYL MONOSTEARATE; PEG-100 STEARATE; PHENYL TRIMETHICONE; MAGNESIUM ALUMINUM SILICATE; TROMETHAMINE; CHOLESTEROL; SODIUM ALGINATE; CELLULOSE, MICROCRYSTALLINE; CARBOXYMETHYLCELLULOSE SODIUM; HYALURONATE SODIUM; TRIETHYL CITRATE; LECITHIN, SOYBEAN; STEARIC ACID; ALUMINUM HYDROXIDE; POLYAMINOPROPYL BIGUANIDE; PHENOXYETHANOL; MICA; IRON; BISMUTH OXYCHLORIDE

DRUG FACTS

ACTIVE INGREDIENT: 2% TITANIUM DIOXIDE

PURPOSE: SUNSCREEN
USE: HELPS PREVENT SUNBURN

WARNINGS:

FOR EXTERNAL USE ONLY

DO NOT USE ON DAMAGED OR BROKEN SKIN

WHEN USING THIS PRODUCT KEEP OUT OF EYES. RINSE WITH WATER TO REMOVE.

STOP USE AND ASK A DOCTOR IF RASH OCCURS

KEEP OUT OF REACH OF CHILDREN. IF PRODUCT IS SWALLOWED, GET MEDICAL HELP OR CONTACT A POISON CONTROL CENTER RIGHT AWAY.

DIRECTIONS

- FOR SUNSCREEN USE:

- APPLY LIBERALLY 15 MINUTES BEFORE SUN EXPOSURE
- REAPPLY AT LEAST EVERY 2 HOURS
- USE A WATER RESISTANT SUNSCREEN IF SWIMMING OR SWEATING
- SUN PROTECTION MEASURES. SPENDING TIME IN THE SUN INCREASES YOUR RISK OF SKIN CANCER AND EARLY SKIN AGING. TO DECREASE THIS RISK, REGULARLY USE A SUNSCREEN WITH A BROAD SPECTRUM SPF VALUE OF 15 OR HIGHER AND OTHER SUN PROTECTION MEASURES INCLUDING:
-
  - LIMIT TIME IN THE SUN, ESPECIALLY FROM 10 AM TO 2 PM
-
  - WEAR LING-SLEEVED SHIRTS, PANTS AND SUNGLASSES
-
  - CHILDREN UNDER 6 MONTHS OF AGE: ASK A DOCTOR

INACTIVE INGREDIENT

INACTIVE INGREDIENTS: water\aqua\eau [] polydecene [] talc [] butylene glycol [] isostearic acid [] glyceryl stearate [] peg-100 stearate [] phenyl trimethicone [] magnesium aluminum silicate [] tromethamine [] cholesterol [] algin [] microcrystalline cellulose [] cellulose gum [] disteardimonium hectorite [] sodium hyaluronate [] triethyl citrate [] lecithin [] stearic acid [] aluminum hydroxide [] polyaminopropyl biguanide [] phenoxyethanol [] [+/- mica [] titanium dioxide (ci 77891) [] iron oxides (ci 77491, ci 77492, ci 77499) [] bismuth oxychloride (ci 77163)

QUESTIONS

PROTECT THE PRODUCT IN THIS CONTAINER FROM EXCESSIVE HEAT AND DIRECT SUN

PACKAGE LABEL

PRINCIPAL DISPLAY PANEL

CLINIQUE

CONTINUOUS

COVERAGE

MAKEUP

BROAD SPECTRUM

SPF 15

NET WT. 1 OZ/ 30 ML

CLINIQUE LABORATORIES DIST
NY NY 10022